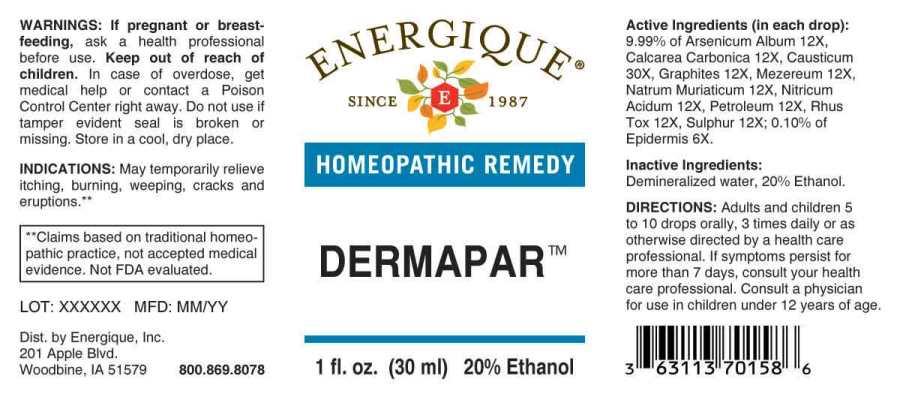 DRUG LABEL: Dermapar
NDC: 44911-0562 | Form: LIQUID
Manufacturer: Energique, Inc.
Category: homeopathic | Type: HUMAN OTC DRUG LABEL
Date: 20240422

ACTIVE INGREDIENTS: SUS SCROFA SKIN 6 [hp_X]/1 mL; ARSENIC TRIOXIDE 12 [hp_X]/1 mL; OYSTER SHELL CALCIUM CARBONATE, CRUDE 12 [hp_X]/1 mL; GRAPHITE 12 [hp_X]/1 mL; DAPHNE MEZEREUM BARK 12 [hp_X]/1 mL; SODIUM CHLORIDE 12 [hp_X]/1 mL; NITRIC ACID 12 [hp_X]/1 mL; KEROSENE 12 [hp_X]/1 mL; TOXICODENDRON PUBESCENS LEAF 12 [hp_X]/1 mL; SULFUR 12 [hp_X]/1 mL; CAUSTICUM 30 [hp_X]/1 mL
INACTIVE INGREDIENTS: WATER; ALCOHOL

DRUG FACTS:

ACTIVE INGREDIENT:

(in each drop): 9.99% of Arsenicum Album 12X, Calcarea Carbonica 12X, Causticum 30X, Graphites 12X, Mezereum12X, Natrum Muriaticum 12X, Nitricum Acidum 12X, Petroleum 12X, Rhus Tox 12X, Sulphur 12X; 0.10% of Epidermis 6X.

INDICATIONS:

May temporarily relieve itching, burning, weeping, cracks and eruptions.**

**Claims based on traditional homeopathic practice, not accepted medical evidence. Not FDA evaluated.

WARNINGS:

If pregnant or breast-feeding, ask a health professional before use.

Keep out of reach of children. In case of overdose, get medical help or contact a Poison Control Center right away.

Do not use if tamper evident seal is broken or missing. Store in a cool, dry place.

KEEP OUT OF REACH OF CHILDREN:

In case of overdose, get medical help or contact a Poison Control Center right away.

DIRECTIONS:

Adults and children 5 to 10 drops orally, 3 time daily or as otherwise directed by a health care professional. If symptoms persist for more than 7 days, consult your health care professional. Consult a physician for use in children under 12 years of age.

INDICATIONS:

May temporarily relieve itching, burning, weeping, cracks and eruptions.**

**Claims based on traditional homeopathic practice, not accepted medical evidence. Not FDA evaluated.

INACTIVE INGREDIENTS:

Demineralized water, 20% Ethanol.

QUESTIONS:

Dist. by Energique, Inc.

201 Apple Blvd

Woodbine, IA 51579 800-869-8078

PACKAGE LABEL DISPLAY:

ENERGIQUE
SINCE 1987
HOMEOPATHIC REMEDY
DERMAPAR
1 fl. oz. (30 ml)